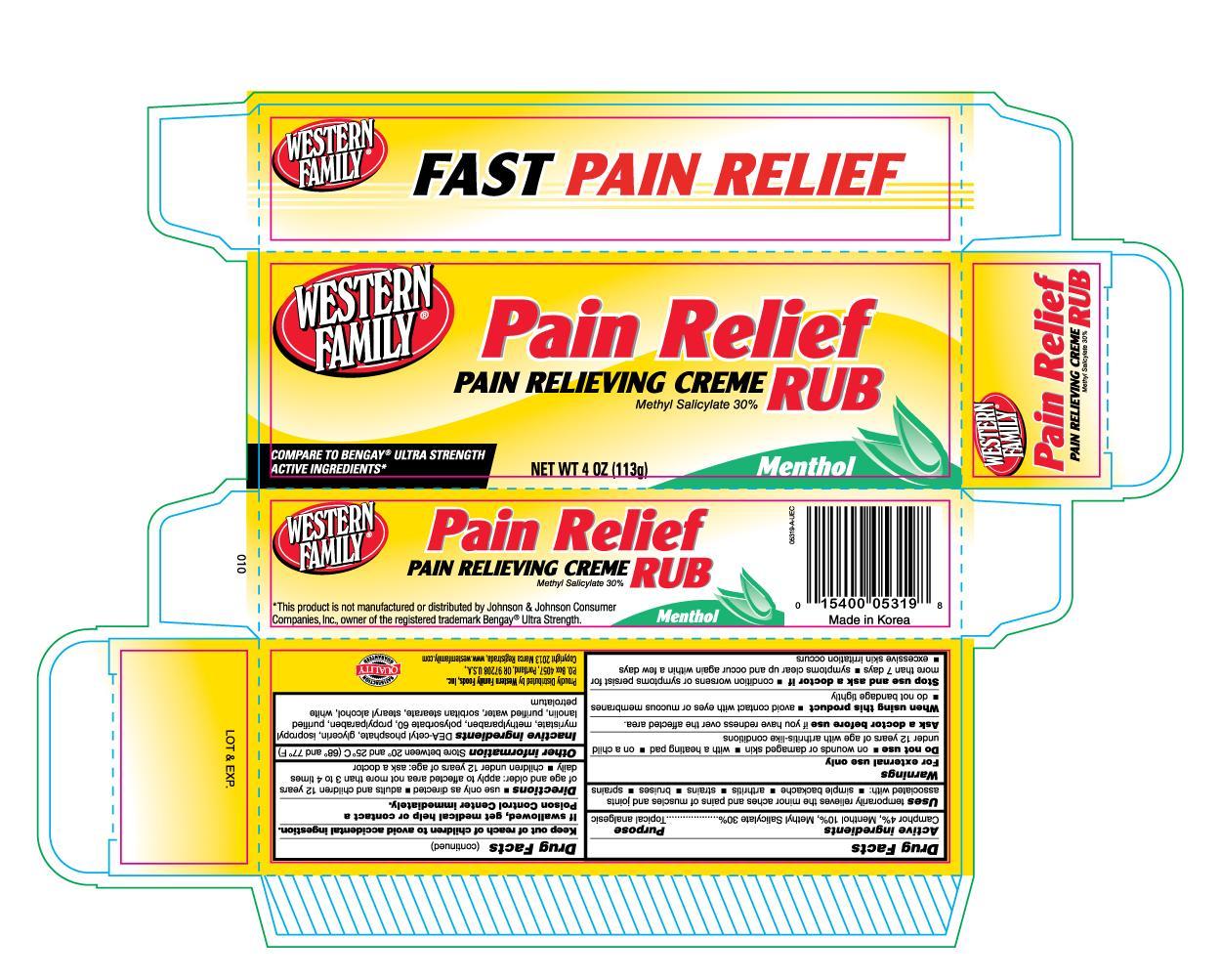 DRUG LABEL: Western Family Pain Relieving
                
NDC: 55312-054 | Form: CREAM
Manufacturer: Western Family Food, Inc.
Category: otc | Type: HUMAN OTC DRUG LABEL
Date: 20130630

ACTIVE INGREDIENTS: CAMPHOR (SYNTHETIC) 0.04 g/1 g; MENTHOL 0.1 g/1 g; METHYL SALICYLATE 0.3 g/1 g
INACTIVE INGREDIENTS: GLYCERIN; ISOPROPYL MYRISTATE; METHYLPARABEN; POLYSORBATE 60; PROPYLPARABEN; LANOLIN; WATER; SORBITAN MONOSTEARATE; STEARYL ALCOHOL; PETROLATUM

Drug Facts

ACTIVE INGREDIENT

Enter section text here

PURPOSE

Uses temporarily relieves the minor aches and pains of muscles and joints associated with:

- simple backache
- arthritis
- strains
- bruises
- sprains

Warnings for external use only.

Do not use

- on wounds or damaged skin
- with a heating pad
- on a child under 12 years of age with arthritis-like conditions

Ask a doctor before use if you have redness over the affected area.

When using this product

- avoid contact with eyes or mucous membranes
- do not bandage tightly

Stop use and ask a doctor if

- condition worsens or symptoms persist for more than 7 days
- symptoms clear up and occur again within a few days
- excessive skin irritation occurs

Keep out of reach of children to avoid accidental ingestion.

- If swallowed, get medical help or contact a Poison Control Center immediately.

Directions

- use only as directed
- adults and children 12 years of age and older: apply area not more than 3 to 4 times daily
- children under 12 years of age: ask a doctor

Other information

- Store between 20° and 25° C (68° and 77° F)

INACTIVE INGREDIENT

Inactive ingredients DEA-cetyl phosphate, glycerin, isopropyl myristate, methylparaben, polysorbate 60, propylparaben, purified lanolin, purified water, sorbitan stearate, stearyl alcohol, white petrolatum

DOSAGE AND ADMINISTRATION

Distributed By:

Western Family Foods, Inc.

P.O. Box 4057

Portland, OR 97208 U.S.A.

Made in Korea